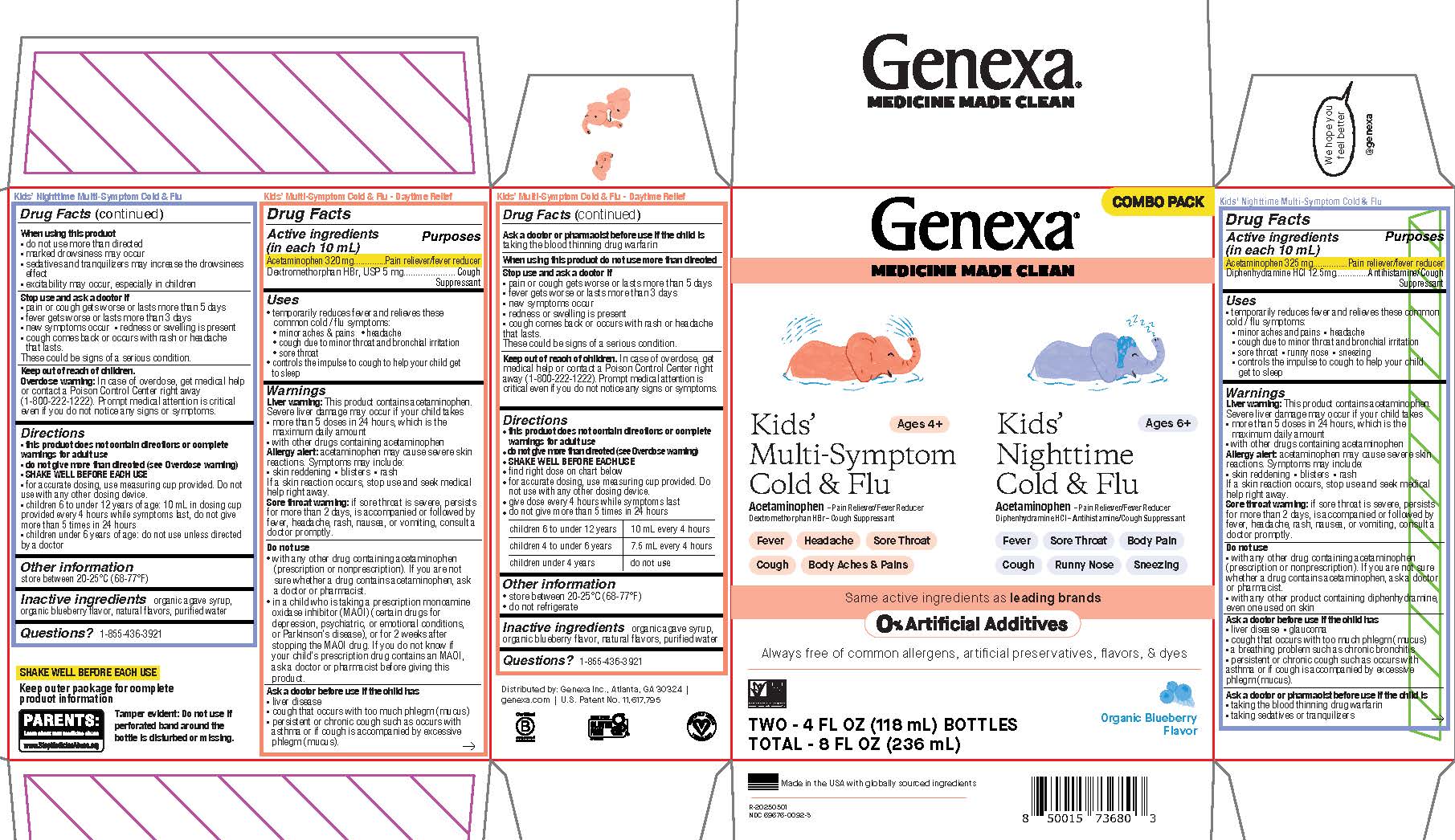 DRUG LABEL: Daytime and Nighttime Kids Multi-Symptom Cold and Flu combo pack
NDC: 69676-0092 | Form: KIT | Route: ORAL
Manufacturer: Genexa Inc.
Category: otc | Type: HUMAN OTC DRUG LABEL
Date: 20251202

ACTIVE INGREDIENTS: DEXTROMETHORPHAN HYDROBROMIDE 5 mg/10 mL; ACETAMINOPHEN 320 mg/10 mL; ACETAMINOPHEN 325 mg/10 mL; DIPHENHYDRAMINE HYDROCHLORIDE 12.5 mg/10 mL
INACTIVE INGREDIENTS: AGAVE TEQUILANA JUICE; BLUEBERRY; WATER; BLUEBERRY; WATER; AGAVE TEQUILANA JUICE

Daytime and Nighttime Kids' Multi-Symptom Cold & Flu Combo pack

Kids' Nighttime Multi-Symptom Cold & Flu

Drug Facts

Active ingredients

(in each 10 mL)

Acetaminophen 325 mg

Diphenhydramine HCl 12.5 mg

Purposes

Pain reliever/fever reducer

Antihistamine/Cough Suppressant

Uses

temporarily reduces fever and relieves these common cold/flu symptoms:

minor aches and pains
headache
cough due to minor throat and bronchial irritation
sore throat
runny nose
sneezing
controls the impulse to cough to help your child get to sleep

Warnings

Liver warning: This product contains acetaminophen. Severe liver damage may occur if your child takes

- more than 5 doses in 24 hours, which is the maximum daily amount
- with other drugs containing acetaminophen

Allergy alert: acetaminophen may cause severe skin reactions. Symptoms may include:

- skin reddening
- blisters
- rash

If a skin reaction occurs, stop use and seek medical help right away.

Sore throat warning: if sore throat is severe, persists for more than 2 days, is accompanied or followed by fever, headache, rash, nausea, or vomiting, consult a doctor promptly.

Do not use

- with any other drug containing acetaminophen (prescription or nonprescription). If you are not sure whether a drug contains acetaminophen, ask a doctor or pharmacist.
- with any other product containing diphenhydramine, even one used on skin

Ask a doctor before use if the child has

- liver disease
- glaucoma
- cough that occurs with too much phlegm (mucus)
- a breathing problem such as chronic bronchitis
- persistent or chronic cough such as occurs with asthma or if cough is accompanied by excessive phlegm (mucus).

Ask a doctor or pharmacist before use if the child is

- taking the blood thinning drug warfarin
- taking sedatives or tranquilizers

When using this product

- do not use more than directed
- marked drowsiness may occur
- sedatives and tranquilizers may increase the drowsiness effect
- excitability may occur, especially in children

Stop use and ask a doctor if

- pain or cough gets worse or lasts more than 5 days
- fever gets worse or lasts more than 3 days
- new symptoms occur
- redness or swelling is present
- cough comes back or occurs with rash or headache that lasts

These could be signs of a serious condition.

Keep out of reach of children.

OVERDOSAGE

Overdose warning: In case of overdose, get medical help or contact a Poison Control Center right away (1-800-222-1222). Prompt medical attention is critical even if you do not notice any signs or symptoms.

Directions

- this product does not contain directions or complete warnings for adult use
- do not give more than directed (see Overdose warning)
- SHAKE WELL BEFORE EACH USE
- for accurate dosing, use measuring cup provided. Do not use with any other dosing device.
- children 6 to under 12 years of age: 10 mL in dosing cup provided every 4 hours while symptoms last, do not give more than 5 times in 24 hours
- children under 6 years of age: do not use unless directed by a doctor

Other information

store between 20-25°C (68-77°F)

Inactive ingredients

organic agave syrup, organic blueberry flavor, natural flavors, purified water

Questions? 1-855-436-3921

SHAKE WELL BEFORE EACH USE

Keep outer package for complete product information

Tamper evident: Do not use if perforated band around the bottle is disturbed or missing.

Kids' Multi-Symptom Cold & Flu - Daytime Relief

Drug Facts

Active ingredients

(in each 10 mL)

Acetaminophen 320 mg

Dextromethorphan HBr, USP 5 mg

Purposes

Pain reliever/fever reducer

Cough Suppressant

Uses

- temporarily reduces fever and relieves these common cold/flu symptoms:
- minor aches & pains
- headache
- cough due to minor throat and bronchial irritation
- sore throat

- controls the impulse to cough to help your child get to sleep

Warnings

Liver warning: This product contains acetaminophen. Severe liver damage may occur if your child takes

- more than 5 doses in 24 hours, which is the maximum daily amount
- with other drugs containing acetaminophen

Allergy alert: acetaminophen may cause severe skin reactions. Symptoms may include:

- skin reddening
- blisters
- rash

If a skin reaction occurs, stop use and seek medical help right away.

Sore throat warning: if sore throat is severe, persists for more than 2 days, is accompanied or followed by fever, headache, rash, nausea, or vomiting, consult a doctor promptly.

Do not use

- with any other drug containing acetaminophen (prescription or nonprescription). If you are not sure whether a drug contains acetaminophen, ask a doctor or pharmacist.
- in a child who is taking a prescription monoamine oxidase inhibitor (MAOI) (certain drugs for depression, psychiatric, or emotional conditions, or Parkinson's disease), or for 2 weeks after stopping the MAOI drug. If you do not know if your child's prescription drug contains an MAOI, ask a doctor or pharmacist before giving this product.

Ask a doctor before use if the child has

- liver disease
- cough that occurs with too much phlegm (mucus)
- persistent or chronic cough such as occurs with asthma or if cough is accompanied by excessive phlegm (mucus).

Ask a doctor or pharmacist before use if the child is taking the blood thinning drug warfarin

When using this product do not use more than directed

Stop use and ask a doctor if

- pain or cough gets worse or lasts more than 5 days
- fever gets worse or lasts more than 3 days
- new symptoms occur
- redness or swelling is present
- cough comes back or occurs with rash or headache that lasts.

These could be signs of a serious condition.

Keep out of reach of children.

OVERDOSAGE

In case of overdose, get medical help or contact a Poison Control Center right away (1-800-222-1222). Prompt medical attention is critical even if you do not notice any signs or symptoms.

Directions

- this product does not contain directions or complete warnings for adult use
- do not give more than directed (see Overdose warning)
- SHAKE WELL BEFORE EACH USE
- find right dose on chart below
- for accurate dosing, use measuring cup provided. Do not use with any other dosing device.
- give dose every 4 hours while symptoms last
- do not give more than 5 times in 24 hours

children 6 to under 12 years | 10 mL every 4 hours
children 4 to under 6 years | 7.5 mL every 4 hours
children under 4 years | do not use

Other information

- store between 20-25°C (68-77°F)
- do not refrigerate

Inactive ingredients

organic agave syrup, organic blueberry flavor, natural flavors, purified water

Questions? 1-855-436-3921

Distributed by: Genexa Inc., Atlanta, GA 30324 |

genexa.com | U.S. Patent No. 11,617,795

Made in the USA with globally sourced ingredients

NDC 69676-0092-3

RECENT MAJOR CHANGES

Kids' Nighttime Multi-Symptom Cold & Flu

Directions

- this product does not contain directions or complete warnings for adult use
- do not give more than directed (see Overdose warning)
- SHAKE WELL BEFORE EACH USE
- for accurate dosing, use measuring cup provided. Do not use with any other dosing device.
- children 6 to under 12 years of age: 10 mL in dosing cup provided every 4 hours while symptoms last, do not give more than 5 times in 24 hours
- children under 6 years of age: do not use unless directed by a doctor

Kids' Multi-Symptom - Daytime Relief

Directions

- this product does not contain directions or complete warnings for adult use
- do not give more than directed (see Overdose warning)
- SHAKE WELL BEFORE EACH USE
- find right dose on chart below
- for accurate dosing, use measuring cup provided. Do not use with any other dosing device.
- give dose every 4 hours while symptoms last
- do not give more than 5 times in 24 hours

children 6 to under 12 years | 10 mL every 4 hours
children 4 to under 6 years | 7.5 mL every 4 hours
children under 4 years | do not use

PACKAGE LABEL

COMBO PACK

Genexa®

MEDICINE MADE CLEAN

Kids' Multi-Symptom Cold & Flu

Ages 4+

Acetaminophen - Pain Reliever/Fever Reducer

Dextromethorphan HBr - Cough Suppressant

Fever

Headache

Sore Throat

Cough

Body Aches & Pains

Kids' Nighttime Cold & Flu

Ages 6+

Acetaminophen - Pain Reliever/Fever Reducer

Diphenhydramine HCl - Antihistamine/Cough Suppressant

Fever

Sore Throat

Body Pain

Cough

Runny Nose

Sneezing

Same active ingredients as leading brands

0% Artificial Additives

Always free of common allergens, artificial preservatives, flavors, & dyes

TWO - 4 FL OZ (118 mL) BOTTLES

TOTAL - 8 FL OZ (236 mL)

Organic Blueberry Flavor